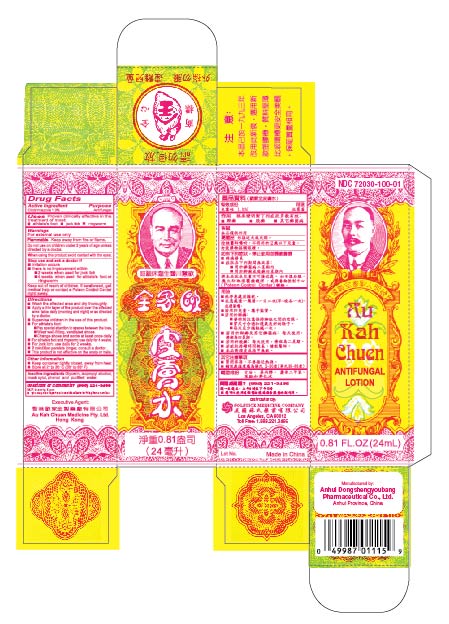 DRUG LABEL: AU KAH CHUEN ANTIFUNGAL
NDC: 72030-100 | Form: LOTION
Manufacturer: ANHUI DONGSHENGYOUBANG PHARMACEUTICAL CO., LTD.
Category: otc | Type: HUMAN OTC DRUG LABEL
Date: 20251118

ACTIVE INGREDIENTS: CLOTRIMAZOLE 1 g/100 mL
INACTIVE INGREDIENTS: GLYCERIN; ISOPROPYL ALCOHOL; MUSK XYLENE; PHENOL; WATER

Drug Facts

Active Ingredient
Clotrimazole 1.0%

Purpose
Antifungal

Uses
Proven clinically effective in the treatment of most:
athlete’s foot
jock itch
ringworm

Warnings
For external use only

Flammable
Keep away from fire or flame.

Do not use on children under 2 years of age unless directed by a doctor.

When using this product avoid contact with the eyes.

Stop use and ask a doctor if
irritation occurs
there is no improvement within:
2 weeks when used for jock itch
4 weeks when used for athlete’s foot or ringworm

Keep out of reach of children. If swallowed, get medical help or contact a Poison Control Center right away.

Directions
Wash the affected area and dry thoroughly.
Apply a thin layer of the product over the affected area twice daily (morning and night) or as directed by a doctor.
Supervise children in the use of this product.
For athlete’s foot:
Pay special attention to spaces between the toes.
Wear well-fitting, ventilated shoes.
Change shoes and socks at least once daily.
For athlete’s foot and ringworm: use daily for 4 weeks.
For jock itch: use daily for 2 weeks.
If condition persists longer, consult a doctor.
This product is not effective on the scalp or nails.

Other Information
Keep container tightly closed, away from heat
Store at 2° to 30° C (36° to 86° F)

Inactive Ingredients
Glycerin, isopropyl alcohol, musk xylol, phenol and purified water.

Questions or Comments? (888) 221-3496M-F, 9am to 5pm
you may also report serious side effects to the phone number.

PACKAGE LABEL

AU KAH CHUEN ANTIFUNGAL LOTION
NDC 72030-100-01
0.81 fl oz (24 mL)